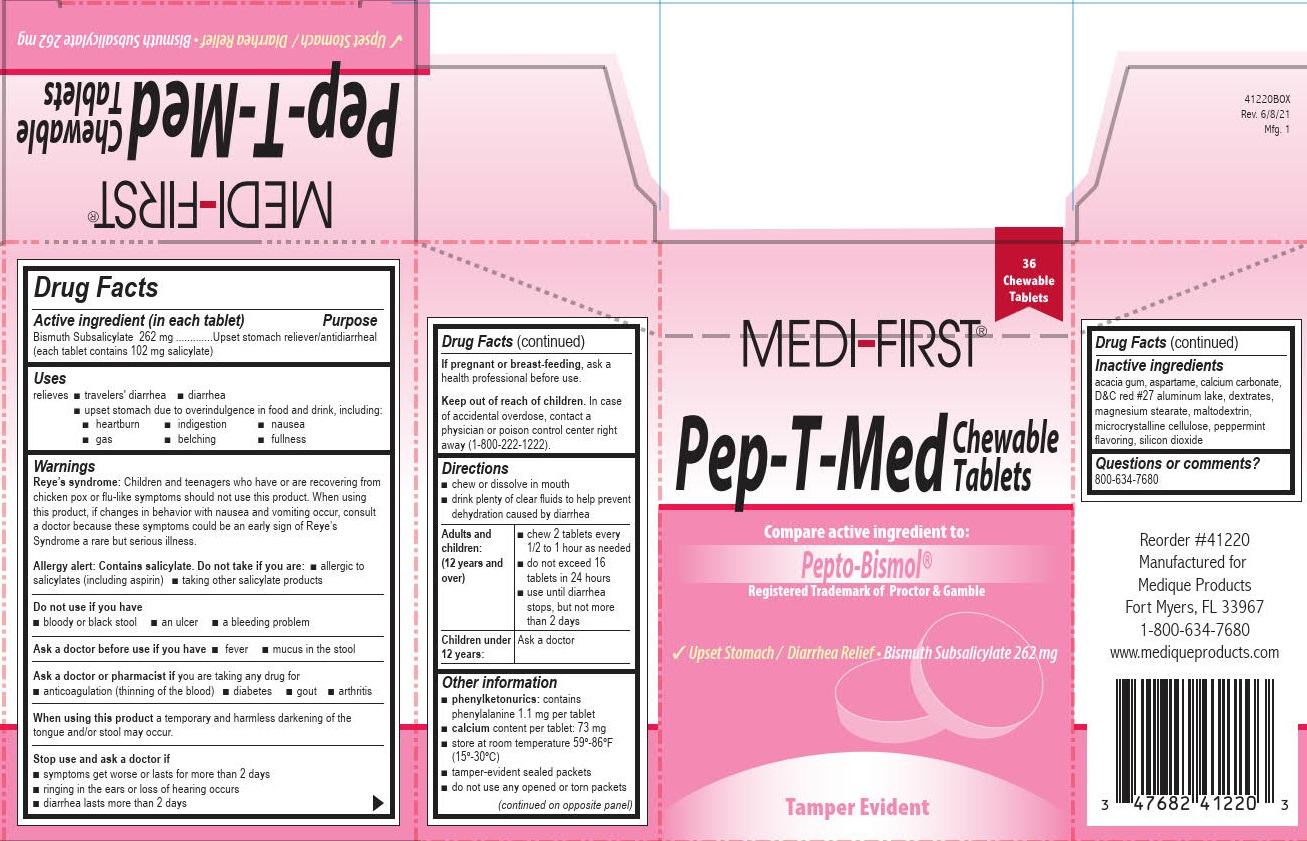 DRUG LABEL: Medi-First Pep-T-Med
NDC: 47682-406 | Form: TABLET, CHEWABLE
Manufacturer: Unifirst First Aid Corporation
Category: otc | Type: HUMAN OTC DRUG LABEL
Date: 20250908

ACTIVE INGREDIENTS: BISMUTH SUBSALICYLATE 262 mg/1 1
INACTIVE INGREDIENTS: ASPARTAME; CALCIUM CARBONATE; CELLULOSE, MICROCRYSTALLINE; D&C RED NO. 27; DEXTRATES; MAGNESIUM STEARATE; SILICON DIOXIDE; ACACIA; MALTODEXTRIN

MEDI-FIRST PEP-T-MED

Drug Facts

Active ingredient (in each tablet)

Bismuth Subsalicylate 262 mg
(each tablet contains 102 mg salicylate)

Purpose

Upset stomach reliever/antidiarrheal

Uses

relieves

- traveler's diarrhea
- diarrhea
- upset stomach due to overindulgence in food and drink, including:
- heartburn
  - indigestion
  - nausea
  - gas
  - belching
  - fullness

Warnings

Reye's syndrome: Children and teenagers who have or are recovering from chicken pox or flu-like symptoms should not use this product. When using this product, if changes in behavior with nausea and vomiting occur, consult a doctor because these symptoms could be an early sign of Reye's Syndrome a rare but serious illness.

Allergy alert: Contains salicylate. Do not take if you are:

- allergic to salicylates (including aspirin)
- taking other salicylate products

Do not use if you have

- bloody or black stool
- an ulcer
- a bleeding problem

Ask a doctor before use if you have

- fever
- mucus in the stool

Ask a doctor or pharmacist if you are taking any drug for

- anticoagulation (thinning of the blood)
- diabetes
- gout
- arthritis

When using this product a temporary and harmless darkening of the tongue and/or stool may occur.

Stop use and ask a doctor if

- symptoms get worse or lasts for more than 2 days
- ringing in the ears or loss of hearing occurs
- diarrhea lasts more than 2 days

PREGNANCY OR BREAST FEEDING

If pregnant or breast-feeding, ask a health professional before use.

Keep out of reach of children.

In case of accidental overdose, contact a physician or poison control center right away (1-800-222-1222).

Directions

- chew or dissolve in mouth
- drink plenty of clear fluids to help prevent dehydration caused by diarrhea

Adults and children: (12 years and over)

- chew 2 tablets every 1/2 to 1 hour as needed
- do not exceed 16 tablets in 24 hours
- use until diarrhea stops, but not more than 2 days

Children under 12 years: Ask a doctor

Children under 12 years: Do not give to children under 12 years of age.

Other information

- phenylketonurics: contains phenylalanine 1.1mg per tablet
- calcium content per tablet: 73 mg
- store at room temperature 59º-86ºF (15º-30ºC)
- tamper-evident sealed packets
- do not use any opened or torn packets

Inactive ingredients

acacia gum, aspartame, calcium carbonate, D&C red #27 aluminum lake, dextrates, magnesium stearate, maltodextrin, microcrystalline cellulose, peppermint flavoring, silicon dioxide

Questions or comments?

1-800-634-7680

Medi-First Pep-T-Med Label

36 Chewable Tablets

Medi-First®

PEP-T-MED

Chewable Tablets

Compare active ingredients to:

Pepto Bismol®

Registered Trademark of Proctor & Gamble

Upset Stomach/Diarrhea Relief • Bismuth Subsalicylate 262mg

Chew or crush tablets completely before swallowing.

Do not swallow tablets whole.

Tamper Evident